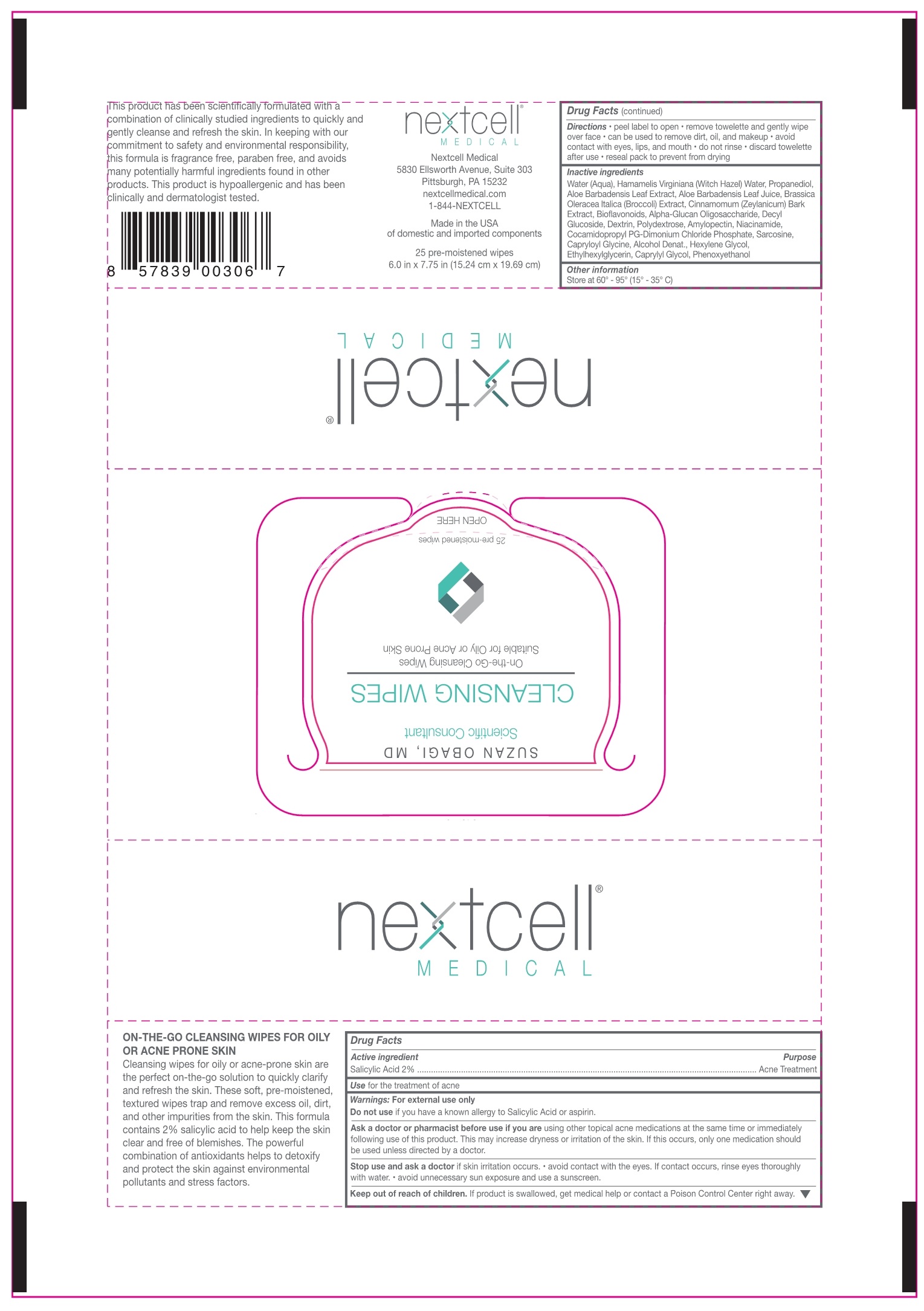 DRUG LABEL: Cleansing Wipes
NDC: 71613-001 | Form: SWAB
Manufacturer: Nextcell Medical
Category: otc | Type: HUMAN OTC DRUG LABEL
Date: 20170728

ACTIVE INGREDIENTS: SALICYLIC ACID 2 g/100 mL
INACTIVE INGREDIENTS: Water; witch hazel; PROPANEDIOL; ALOE VERA LEAF; BRASSICA OLERACEA VAR. ITALICA WHOLE; CITRUS BIOFLAVONOIDS; .ALPHA.-GLUCAN OLIGOSACCHARIDE; DECYL GLUCOSIDE; ICODEXTRIN; Polydextrose; AMYLOPECTIN; Niacinamide; COCAMIDOPROPYL PG-DIMONIUM CHLORIDE PHOSPHATE; SARCOSINE; CAPRYLOYL GLYCINE; ALCOHOL; HEXYLENE GLYCOL; ETHYLHEXYLGLYCERIN; CAPRYLYL GLYCOL; PHENOXYETHANOL; CINNAMON BARK OIL

Active Ingredient

Salicylic Acid 2%

Purpose

Acne Treatment

Use

For the treatment of acne

Warnings

- For external use only
- Do not use if you have a known allergy to salicylic acid or asprin
- Ask a doctor or pharmacist before use if you are using other topical acne medications at the same time or immediately following the use of this product. This may increase dryness or irritation of the skin. If this occurs, only one medication should be used unless directed by a doctor.
- Stop use and ask a doctor if skin irritation occurs.
- Avoid contact with eyes. If contact occursm rinse eyes thoroughly with water.
- Avoid any uncessary sun exposure and use a sunscreen.

Keep out of reach of children

If product is swallowed, get medical help or contact a Poison Control Center right away.

Directions

- peel label to open
- remove towlette and gently wipe over faace
- can be used to remove dirt, oil, and makeup
- avoid contact with eyes lips and mouth
- do not rinse
- discard towlette after use
- reseal pack to prevent from drying

Inactive ingredients

Alcohol, Aloe Barbadensis Leaf Extract, Aloe Barbadensis Leaf Juice, Alpha-Glucan Oligosaccharide, Amylopectin, Bioflavonoids, Brassica Oleracea, Italica (Broccoli) Extract, Capryloyl Glycine, Caprylyl Glycol, Cinnamomum Zeylanicum Barck Extract, Cocoamidopropyl PG-Dimonium, Chloride Phosphate, Decyl Glucoside, Dextrin, Ethylhexylglycerin, Hamamelis Virginiana (Witch Hazel) Water, Hexylene Glycol, Niacinamide, Phenoxyethanol, Polydextrose, Propanediol, Sarcosine, Water